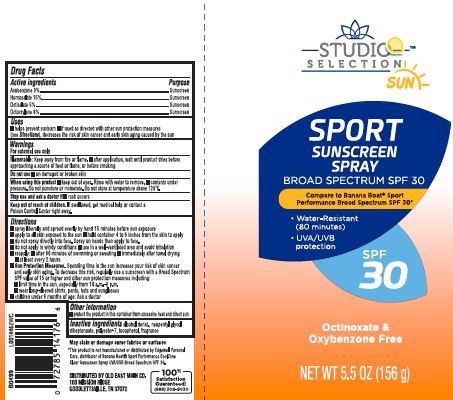 DRUG LABEL: Sunscreen
NDC: 55910-564 | Form: SPRAY
Manufacturer: Old East Main Co.
Category: otc | Type: HUMAN OTC DRUG LABEL
Date: 20260302

ACTIVE INGREDIENTS: AVOBENZONE 30 mg/1 g; HOMOSALATE 150 mg/1 g; OCTISALATE 50 mg/1 g; OCTOCRYLENE 80 mg/1 g
INACTIVE INGREDIENTS: ALCOHOL; NEOPENTYL GLYCOL DIHEPTANOATE; POLYESTER-7; TOCOPHEROL

Studio Selection 083.000/083AA
Sport Sunscreen Spray SPF 30

active ingredients

Avobenzone 3%

Homosalate 15%

Octisalate 5%

Octocrylene 8%

purpose

Sunscreen

use

■ helps prevent sunburn
■ if used as directed with other sun protection measures (see Directions), decreases the risk of skin cancer and early skin aging caused by the sun

Warnings

For external use only

Flammable

Keep away from fire or flame

- after application, wait until product dries before approaching a source of heat or flame, or before smoking

Do not use

on damaged or broken skin

When using this product

- Keep out of eyes. Rinse with water to remove.
- contents under pressure. Do not pumcture or incinerate. Do not store at temperature above 120ºF.

Stop use and ask a doctor if

- rash occurs

Keep out of reach of children.

If swallowed, get medical help or contact a Poison Control Center right away.

Directions

■ spray liberally and spread evenly by hand 15 minutes before sun exposure
■ apply to all skin exposed to the sun
■ hold container 4 to 6 inches from the skin to apply
■ do not spray directly into face. Spray on hands then apply to face.
■ do not apply in windy conditions
■ use in a well-ventilated area and avoid inhalation
■ reapply:
■ after 80 minutes of swimming or sweating
■ immediately after towel drying
■ at least every 2 hours
■ Sun Protection Measures. Spending time in the sun increases your risk of skin cancer and early skin aging. To decrease this risk, regularly use a sunscreen with a Broad Spectrum SPF value of 15 or higher and other sun protection measures including:
■ limit time in the sun, especially from 10 a.m.–2 p.m.
■ wear long-sleeved shirts, pants, hats and sunglasses
■ children under 6 months of age: Ask a doctor

other information

- protect the product in this container from excessive heat and direct sun

inactive ingredient

alcohol denat., neopentyl glycol diheptanoate, polyester-7, tocopherol, fragrance

Disclaimers

May stain or damage some fabrics or surfaces

*This product is not manufactured or distributed by Edgewell Personal Care, distributor of Banana BoatSport Performance CoolZone Clear Sunscreen Spray UVA/UVB Broad Spectrum SPF 30

ADVERSE REACTION

100% Satisfaction Guaranteed!

(888)309-9030

DISTRIBUTED BY OLD EAST MAIN CO

100 MISSION RIDGE

GOODLETTSVILLE, TN 37072

PRINCIPAL DISPLAY PANEL

STUDIO SELECTION™

SUN SPORT SUNSCREEN SPRAY

BROAD SPECTRUM SPF 30

Compare to Banana Boat®Sport Performance Broad Spectrum SPF 30*

- Water-resistant (80 minutes)
- UVA/UVB protection

SPF 30

Octinoxate, Oxybenzone & Paraben Free

NET WT 5.5 OZ (156 g)